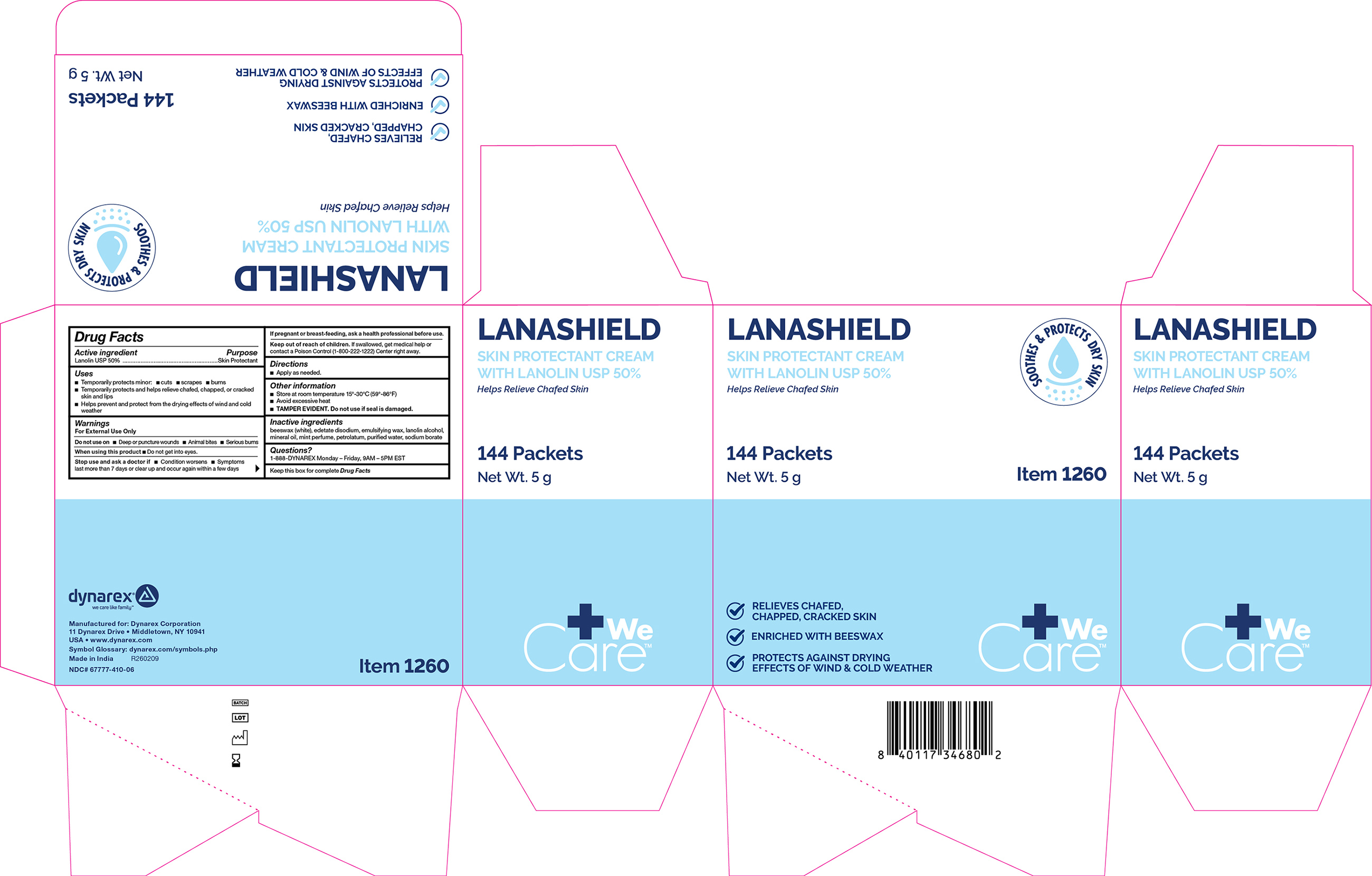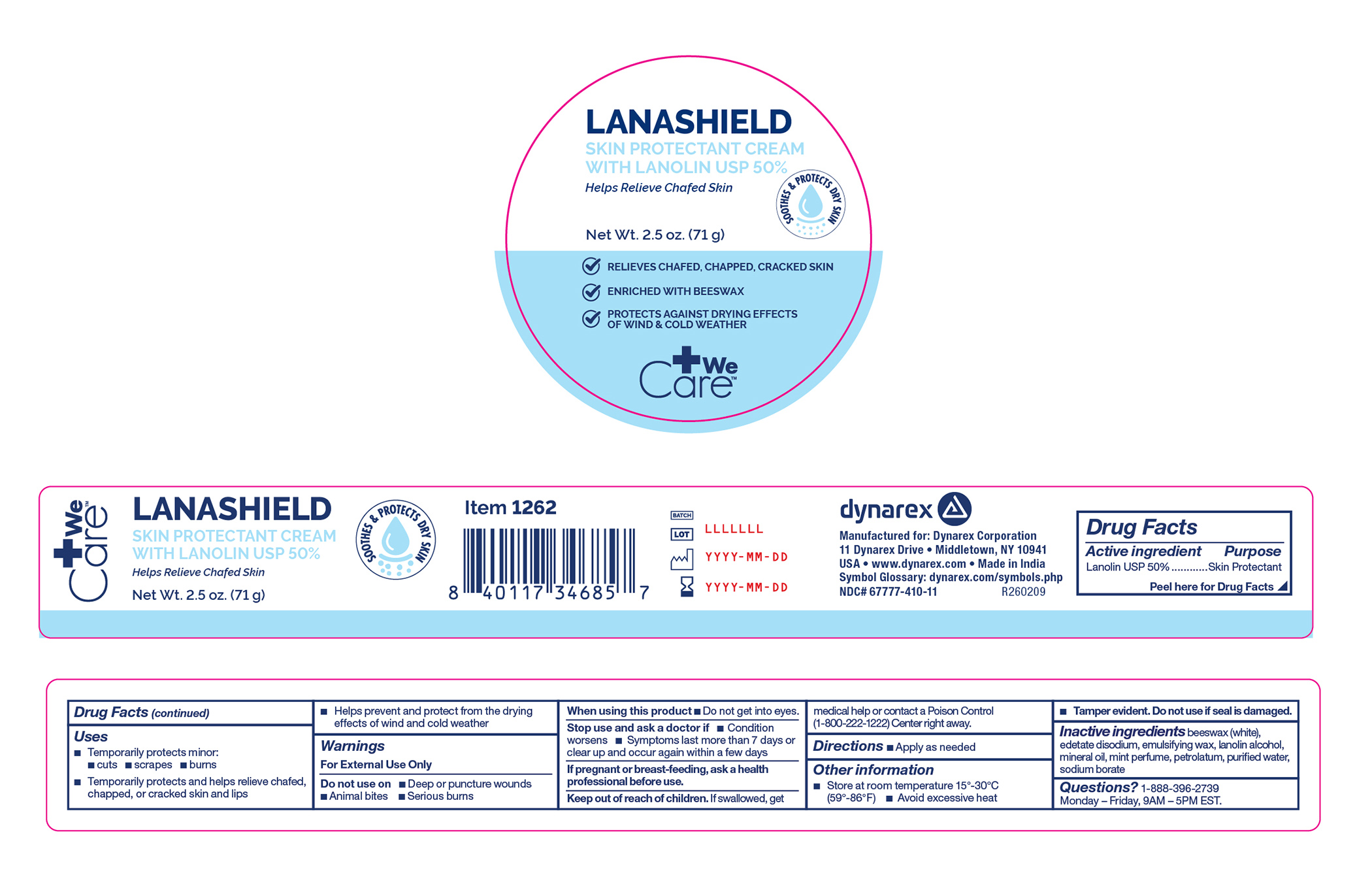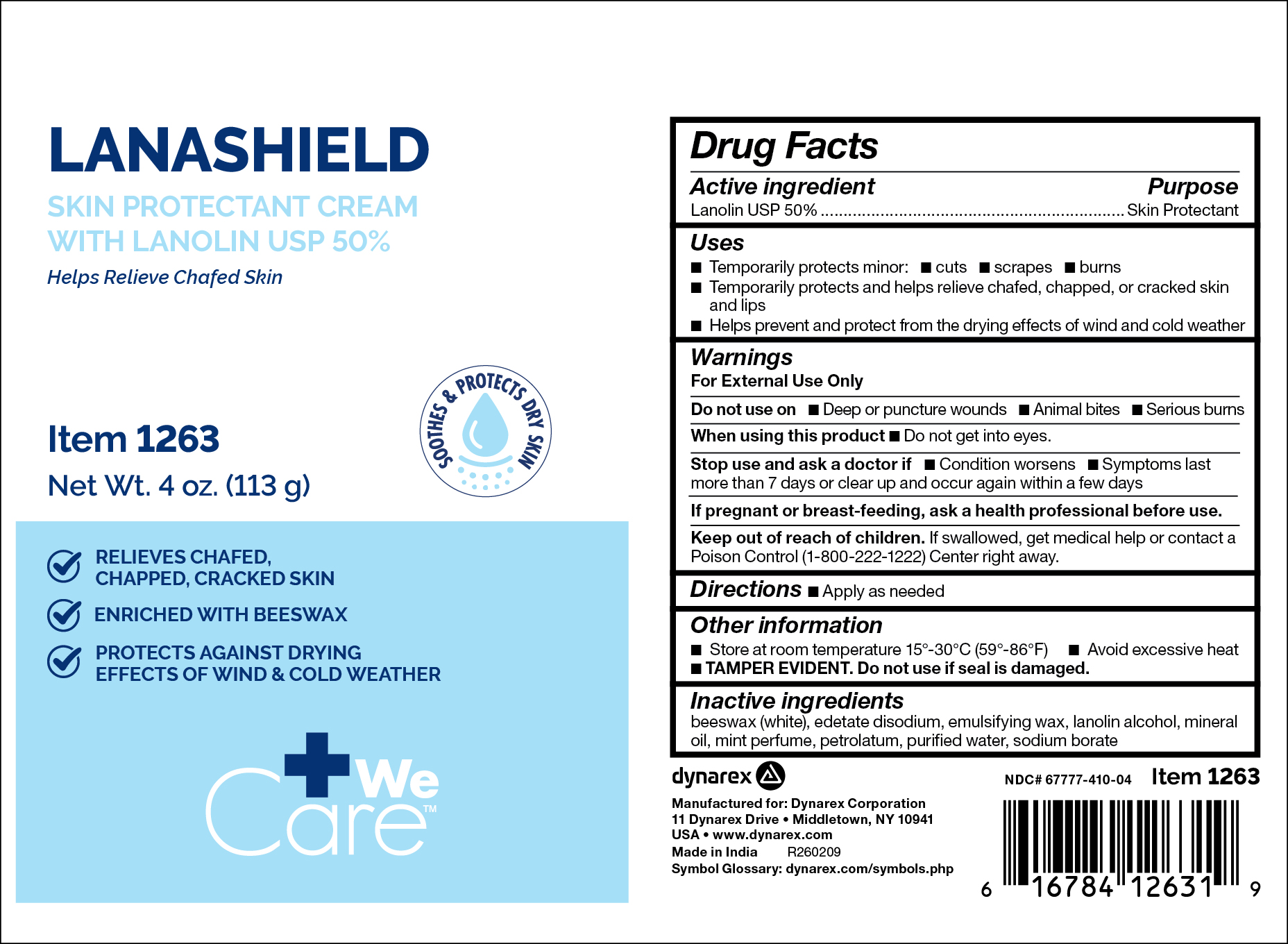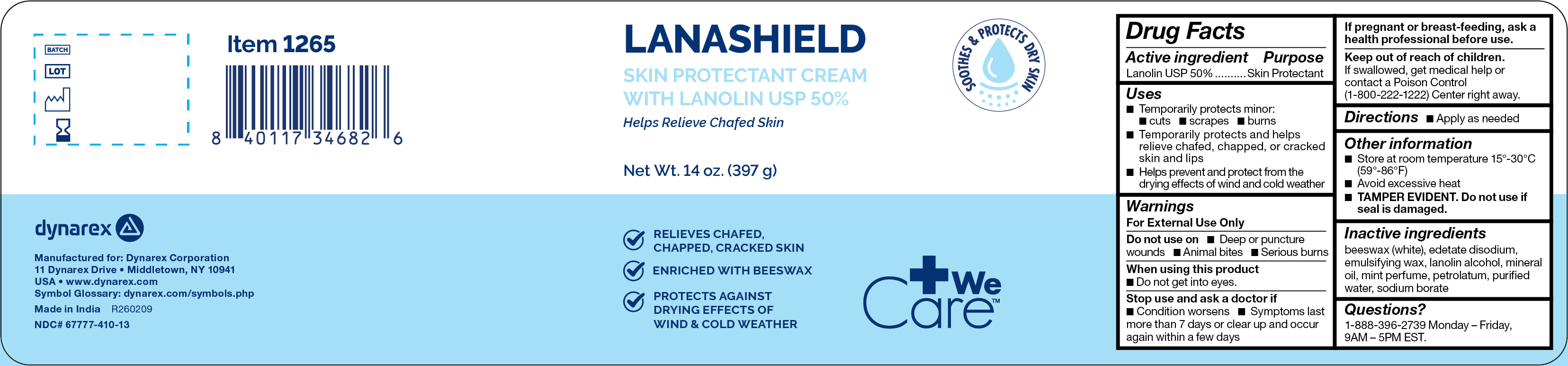 DRUG LABEL: Lanashield
NDC: 67777-410 | Form: OINTMENT
Manufacturer: Dynarex Corporation
Category: otc | Type: HUMAN OTC DRUG LABEL
Date: 20260226

ACTIVE INGREDIENTS: LANOLIN 50 g/100 g
INACTIVE INGREDIENTS: LANOLIN ALCOHOLS; WHITE WAX; MINERAL OIL; SODIUM BORATE; WATER; EDETATE DISODIUM; WHITE PETROLATUM

1260
1262
1263
1265

Active Ingredient

Lanolin USP 50%

Purpose

Skin Protectant

Uses

- Temporarily protects minor • cuts • scrapes • burns
- Temporarily protects and helps relieve chafed, chapped, or cracked skin and lips
- Helps prevent and protect from the drying effects of wind and cold weather

Warnings

For External Use Only

Do not use on

• Deep or puncture wounds • Animal bites • Serious burns

When using this product

• Do not get into eyes.

Stop use and ask a doctor if

• Condition worsens • Symptoms last more than 7 days or clear up and occur again within a few days

PREGNANCY OR BREAST FEEDING

If pregnant or breast-feeding, ask a health professional before use.

Keep out of reach of children.

If swallowed, get medical help or contact a Poison Control (1-800-222-1222) Center right away.

Directions

Apply as needed

Other Information

- Store at room temperature 15º-30ºC (59º-86ºF)
- Avoid excessive heat
- Tamper evident. Do not use if seal is damaged.

Inactive Ingredients

beeswax (White), edetate disodium, emulsifying wax, lanolin alcohol, mineral oil, mint perfume, petrolatum, purified water, sodium borate